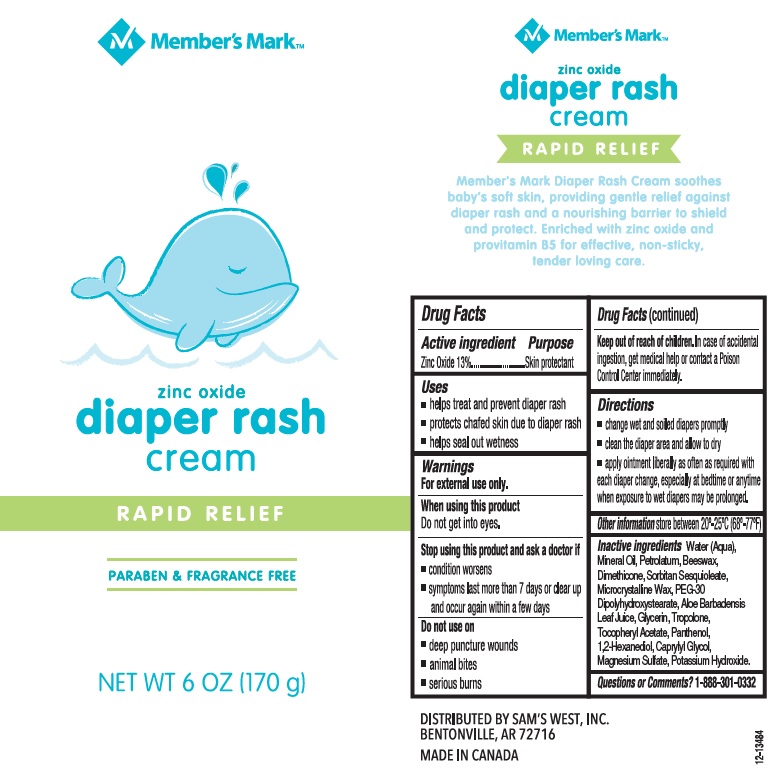 DRUG LABEL: Members Mark Diaper Rash
NDC: 68196-002 | Form: CREAM
Manufacturer: Sams West Inc
Category: otc | Type: HUMAN OTC DRUG LABEL
Date: 20180321

ACTIVE INGREDIENTS: ZINC OXIDE 13 g/100 g
INACTIVE INGREDIENTS: WATER; MINERAL OIL; PETROLATUM; YELLOW WAX; DIMETHICONE; SORBITAN SESQUIOLEATE; MICROCRYSTALLINE WAX; PEG-30 DIPOLYHYDROXYSTEARATE; ALOE VERA LEAF; GLYCERIN; TROPOLONE; .ALPHA.-TOCOPHEROL ACETATE, DL-; PANTHENOL; 1,2-HEXANEDIOL; CAPRYLYL GLYCOL; MAGNESIUM SULFATE, UNSPECIFIED FORM; POTASSIUM HYDROXIDE

Drug Facts

Active ingredient

Zinc Oxide 13%

Purpose

Skin protectant

Uses

- helps treat and prevent diaper rash
- protects chafed skin due to diaper rash
- helps seal out wetness

Warnings

For external use only.

When using this product

Do not get into eyes.

Stop using this product and ask a doctor if

- condition worsens
- symptoms last more than 7 days or clear up and occur again within a few days.

Do not use on

- deep puncture wounds
- animal bites
- serious burns

Keep out of reach of children.

In case of accidental ingestion, get medical help or contact a Poison Control Center immediately.

Directions

- change wet and soiled diapers promptly
- clean the diaper area and allow to dry
- apply ointment liberally as often as required with each diaper change, especially at bedtime or anytime when exposure to wet diapers may be prolonged.

Other information

store between 20°C - 25°C (68°F - 77°F)

Inactive ingredients

Water (Aqua), Mineral Oil, Petrolatum, Beeswax, Dimethicone, Sorbitan Sesquioleate, Microcrystalline Wax, PEG-30 Dipolyhydroxystearate, Aloe Barbadensis Leaf Juice, Glycerin, Tropolone, Tocopheryl Acetate, Panthenol, 1,2-Hexanediol, Caprylyl Glycol, Magnesium Sulfate, Potassium Hydroxide.

Questions or comments?

1-888-301-0332